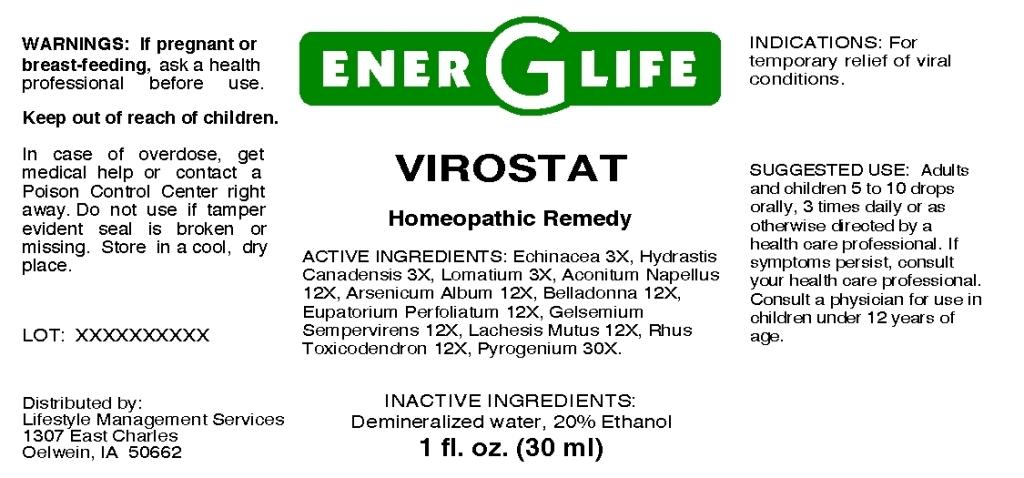 DRUG LABEL: Virostat
NDC: 57520-0657 | Form: LIQUID
Manufacturer: Apotheca Company
Category: homeopathic | Type: HUMAN OTC DRUG LABEL
Date: 20110330

ACTIVE INGREDIENTS: ECHINACEA 3 [hp_X]/1 mL; GOLDENSEAL 3 [hp_X]/1 mL; LOMATIUM DISSECTUM ROOT 3 [hp_X]/1 mL; ACONITUM NAPELLUS 12 [hp_X]/1 mL; ARSENIC TRIOXIDE 12 [hp_X]/1 mL; ATROPA BELLADONNA 12 [hp_X]/1 mL; EUPATORIUM PERFOLIATUM FLOWERING TOP 12 [hp_X]/1 mL; GELSEMIUM SEMPERVIRENS ROOT 12 [hp_X]/1 mL; LACHESIS MUTA VENOM 12 [hp_X]/1 mL; TOXICODENDRON PUBESCENS LEAF 12 [hp_X]/1 mL; RANCID BEEF 30 [hp_X]/1 mL
INACTIVE INGREDIENTS: WATER; ALCOHOL

Virostat

ACTIVE INGREDIENT

ACTIVE INGREDIENTS: Echinacea 3X, Hydrastis canadensis 3X, Lomatium 3X, Aconitum napellus 12X, Arsenicum album 12X, Belladonna 12X, Eupatorium perfoliatum 12X, Gelsemium sempervirens 12X, Lachesis mutus 12X, Rhus toxicodendron 12X, Pyrogenium 30X.

PURPOSE

INDICATIONS: For temporary relief of viral conditions.

WARNINGS

WARNINGS: If pregnant or breast-feeding, ask a health professional before use.

Keep out of reach of children. In case of overdose, get medical help or contact a Poison Control Center right away.

Do not use if tamper evident seal is broken or missing. Store in a cool, dry place.

DOSAGE AND ADMINISTRATION

SUGGESTED USE: Adults and children 5 to 10 drops orally, 3 times daily or as otherwise directed by a health care professional. If symptoms persist, consult your health care professional. Consult a physician for use in children under 12 years of age.

INACTIVE INGREDIENTS: Demineralized water, 20% Ethanol.

KEEP OUT OF REACH OF CHILDREN. In case of overdose, get medical help or contact a Poison Control Center right away.

INDICATIONS: For temporary relief of viral conditions.

QUESTIONS

Distributed by:

Lifestyle Management Services

1307 East Charles

Oelwein, IA 50662

PACKAGE LABEL

ENER G LIFE

VIROSTAT

Homeopathic Remedy

1 fl. oz. (30 ml)